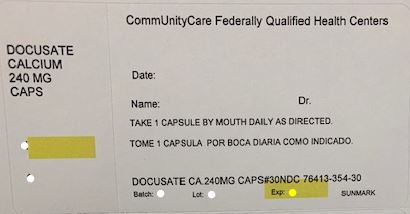 DRUG LABEL: Stool Softener
NDC: 76413-354 | Form: CAPSULE, LIQUID FILLED
Manufacturer: Central Texas Community Health Centers
Category: otc | Type: HUMAN OTC DRUG LABEL
Date: 20181128

ACTIVE INGREDIENTS: DOCUSATE CALCIUM 240 mg/1 1
INACTIVE INGREDIENTS: CORN OIL; D&C RED NO. 33; FD&C BLUE NO. 1; FD&C RED NO. 40; FD&C YELLOW NO. 6; GELATIN, UNSPECIFIED; GLYCERIN; WATER; SORBITOL; SORBITAN

Drug Facts

Active ingredient (in each softgel)

Docusate calcium 240 mg

Purpose

Stool softener laxative

Uses

- for relief of occasional constipation
- this product generally produces a bowel movement within 12 to 72 hours

Warnings

Do not use

if you are currently taking mineral oil, unless directed by a doctor.

Ask a doctor before use if you have

- stomach pain
- nausea
- vomiting
- noticed a sudden change in bowel habits that lasts over 2 weeks

Stop use and ask a doctor if

- you have rectal bleeding or fail to have a bowel movement after use of a laxative. These could be signs of a serious condition.
- you need to use a laxative for more than 1 week

If pregnant or breast-feeding,

ask a health professional before use.

Keep out of reach of children.

In case of overdose, get medical help or contact a Poison Control Center right away.

Directions

- adults and children 12 years of age and over: take 1 softgel daily or as directed by a doctor
- children under 12 years of age: ask a doctor

Other information

- store between 20-25ºC (68-77ºF); excursions permitted between 15-30ºC (59-86ºF)

Inactive ingredients

corn oil, D&C red #33*, edible white ink, FD&C blue #1, FD&C red #40, FD&C yellow #6, gelatin, glycerin, purified water, sorbitol special

*contains one or more of these ingredients

Questions or comments?

Call 1-877-753-3935 Monday-Friday 9AM-5PM EST

HOW SUPPLIED

Product: 76413-354

NDC: 76413-354-30 30 CAPSULE, LIQUID FILLED in a BOTTLE, PLASTIC